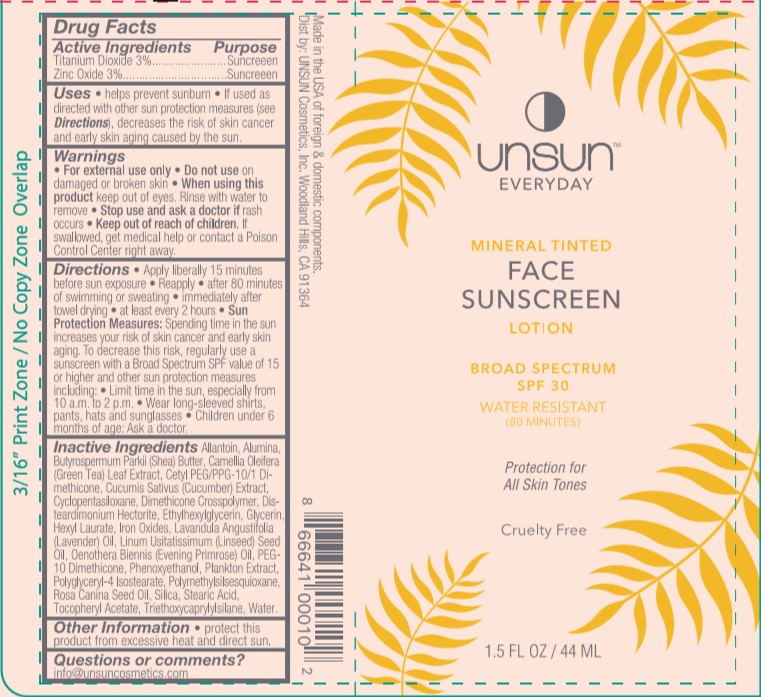 DRUG LABEL: Unsun
NDC: 58443-0306 | Form: LOTION
Manufacturer: Prime Enterprises Inc.
Category: otc | Type: HUMAN OTC DRUG LABEL
Date: 20201021

ACTIVE INGREDIENTS: TITANIUM DIOXIDE 31.5 mg/1 mL; ZINC OXIDE 31.5 mg/1 mL
INACTIVE INGREDIENTS: PHYSALIS ANGULATA; CUCUMBER SEED; POLYMETHYLSILSESQUIOXANE (4.5 MICRONS); ROSA CANINA SEED; DIMETHICONE CROSSPOLYMER (450000 MPA.S AT 12% IN CYCLOPENTASILOXANE); DISTEARDIMONIUM HECTORITE; HEXYL LAURATE; CETYL PEG/PPG-10/1 DIMETHICONE (HLB 2); LINSEED OIL; ALPHA-TOCOPHEROL ACETATE; EVENING PRIMROSE OIL; CYCLOMETHICONE 5; PHENOXYETHANOL; GLYCERIN; LAVENDER OIL; ALLANTOIN; PEG-10 DIMETHICONE (600 CST); SILICON DIOXIDE; ALUMINUM OXIDE; WATER; CAMELLIA OLEIFERA LEAF; POLYGLYCERYL-4 ISOSTEARATE; ETHYLHEXYLGLYCERIN; STEARIC ACID; SHEA BUTTER; FERRIC OXIDE RED; TRIETHOXYCAPRYLYLSILANE

Unsun face Sunscreen Broad Spectrum SPF 30

Active Ingredients

Titanium Dioxide 3%, Zinc Oxide 3%

Purpose

Sunscreen

Uses

helps prevent sunburn

If used as directed with other sun protection measures (see Directions), decreases the risk of skin cancer and early skin aging caused by the sun.

Warnings

For external use only

Do not use

on damaged or broken skin

When using this product

keep out of eyes. Rinse with water to remove

Stop use and ask a doctor if

rash occurs

Keep out of reach of children.

If swallowed, get medical help or contact a Poison Control Center right away.

Directions

Apply liberally 15 minutes before sun exposure

Reapply

after 80 minutes of swimming or sweating

immediately after towel drying

at least every 2 hours

Sun Protection Measures: Spending time in the sun increases your risk of skin cancer and early skin aging. To decrease this risk, regularly use a sunscreen with a Broad Spectrum SPF value of 15 or higher and other sun protection measures including:

Limit time in the sun, especially from 10 a.m. to 2 p.m.

Wear long-sleeved shirts, pants, hats, and sunglasses

Children under 6 months of age: Ask a doctor.

Inactive Ingredients

Allantoin, Alumina, Butyrospermum Parkii (Shea) Butter, Camellia Oleifera (Green Tea) Leaf Extract, Cetyl PEG/PPG-10/1 Dimethicone, Cucumis Sativus (Cucumber) Extract, Cyclopentasiloxane, Dimethicone Crosspolymer, Disteardimonium Hectorite, Ethylhexylglycerin, Glycerin, Hexyl Laurate, Iron Oxides, Lavandula Angustifolia (Lavender) Oil, Linum Usitatissimum (Linseed) Seed Oil, Oenothera Biennis (Evening Primrose) Oil, PEG-10 Dimethicone, Phenoxyethanol, Plankton Extract, Polyglyceryl-4 Isostearate, Polymethylsilsesquioxane, Rosa Canina Seed Oil, Silica, Stearic Acid, Tocopheryl Acetate, Triethoxycaprylylsilane, Water

Other Information

protect this product from excessive heat and direct sun.

Questions or comments?

info@unsuncosmetics.com